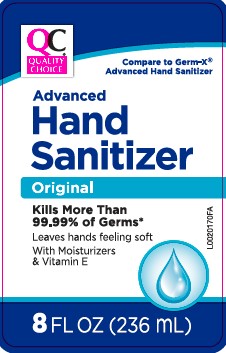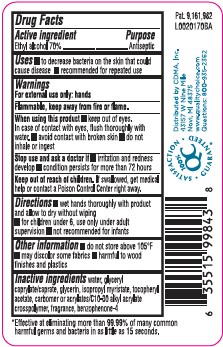 DRUG LABEL: Advanced Hand Sanitizer
NDC: 63868-882 | Form: GEL
Manufacturer: Chain Drug Marketing Association
Category: otc | Type: HUMAN OTC DRUG LABEL
Date: 20260219

ACTIVE INGREDIENTS: ALCOHOL 70 mL/100 mL
INACTIVE INGREDIENTS: WATER; GLYCERYL CAPRYLATE/CAPRATE; GLYCERIN; ISOPROPYL MYRISTATE; .ALPHA.-TOCOPHEROL ACETATE; CARBOMER COPOLYMER TYPE B (ALLYL PENTAERYTHRITOL CROSSLINKED); SULISOBENZONE

Quality Choice 370.001/370AB & AE rev 1
Advanced Hand Sanitizer

Active Ingredient

Ethyl alcohol 70%

Purpose

Antiseptic

Uses

- to decrease bacteria on the skin that could cause disease
- recommended for repeated use

Warnings

For external use only: hands

Flammable, keep away from fire or flame.

When using this product

- keep out of eyes. In case of contact with eyes, flush thoroughly with water.
- avoid contact with broken skin
- do not inhale or ingest

Stop use and ask a doctor if

- irritation and redness develop
- condition persists for more than 72 hours

Keep out of reach of children.

If swallowed, get medical help or contact a Poison Control Center right away.

Directions

- wet hands thoroughly with product and allow to dry without wiping
- for children under 6, use only under adult supervision
- not recommended for infants

Other information

- do not store above 105⁰F
- may discolor some fabrics
- harmful to wood finishes and plastics

Inactive ingredients

water, glyceryl caprylate/caprate, glycerin, isopropyl myristate, tocopheryl acetate, acrylates/C10-30 alkyl acrylate crosspolymer, fragrance, benzophenone-4

ADVERSE REACTION

*Effective at eliminating more than 99.99% of many common harmful germs and bacteria in as little as 15 seconds

Distributed by CDMA, Inc.

43157 W Nine Mile

Novi, MI 48357

www.qualitychoice.com

Questions: 800-935-2362

100% QC

SATISFACTION GUARANTEED

Pat. 9,161,982

principal display panel

QC®

Quality Choice

Compare to Germ-X®Advanced Hand Sanitizer

Advanced Hand Sanitizer

Original

Kills More Than 99.99% of Germs*

Leaves hands feeling soft

With Moisturizers & Vitamin E

8 FL OZ (236 mL)